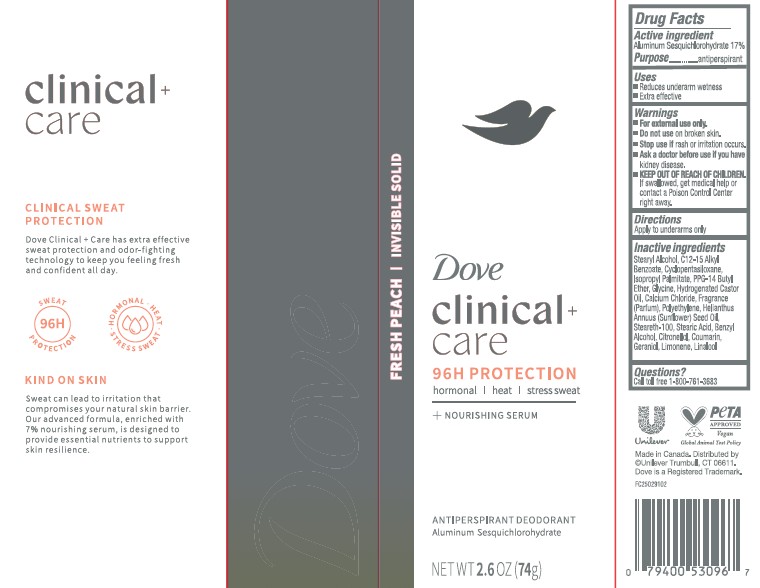 DRUG LABEL: Dove
NDC: 64942-2383 | Form: STICK
Manufacturer: Conopco Inc. d/b/a/ Unilever
Category: otc | Type: HUMAN OTC DRUG LABEL
Date: 20251002

ACTIVE INGREDIENTS: ALUMINUM SESQUICHLOROHYDRATE 17 g/100 g
INACTIVE INGREDIENTS: GLYCINE; CYCLOPENTASILOXANE; GERANIOL; PPG-14 BUTYL ETHER; STEARIC ACID; BENZYL ALCOHOL; C12-15 ALKYL BENZOATE; HYDROGENATED CASTOR OIL; CALCIUM CHLORIDE; STEARETH-100; CITRONELLOL; COUMARIN; LINALOOL; STEARYL ALCOHOL; POLYETHYLENE; ISOPROPYL PALMITATE; HELIANTHUS ANNUUS (SUNFLOWER) SEED OIL; LIMONENE, (+)-

Dove Clinical + Care 96H Protection Fresh Peach Invisible Solid Antiperspirant Deodorant

DESCRIPTION

Dove Clinical + Care 96H Protection Fresh Peach Invisible Solid Antiperspirant Deodorant

ACTIVE INGREDIENT

Aluminum Sesquichlorohydrate 17%

PURPOSE

Antiperspirant

INDICATIONS AND USAGE

Reduces underarm wetness
Extra effective

WARNINGS

For external use only.
• Do not use on broken skin.• Stop use if rash or irritation occurs. • Ask a doctor before
use if you have kidney disease

Keep out of reach of children. If swallowed,get medical help or contact a Poison Control Center right away.

DOSAGE AND ADMINISTRATION

Apply to underarms only

INACTIVE INGREDIENT

Stearyl Alcohol, C12-15 Alkyl Benzoate, Cyclopentasiloxane, Isopropyl Palmitate, PPG-14 Butyl Ether, Glycine, Hydrogenated Castor Oil,Calcium Chloride, Polyethylene, Helianthus Annuus (Sunflower) Seed Oil, Steareth-100, Stearic Acid, Benzyl Alcohol, Citronellol, Coumarin, Geraniol, Limonene, Linalool

QUESTIONS

call 1-800-761-3683